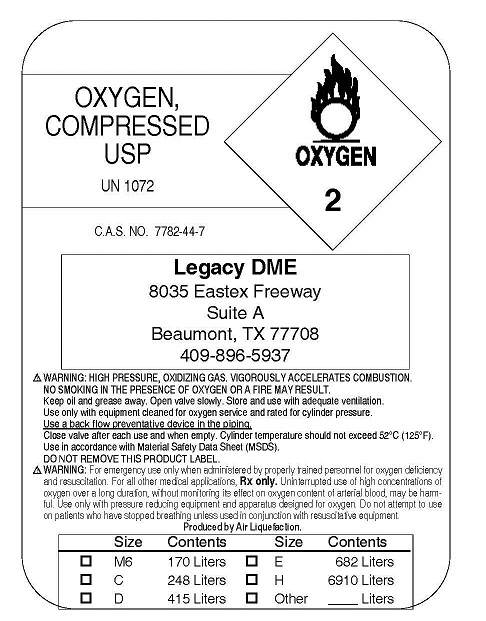 DRUG LABEL: Oxygen
NDC: 52087-0001 | Form: GAS
Manufacturer: Legacy Durable Medical Equipment Inc
Category: prescription | Type: HUMAN PRESCRIPTION DRUG LABEL
Date: 20100312

ACTIVE INGREDIENTS: Oxygen 99 L/100 L

Oxygen